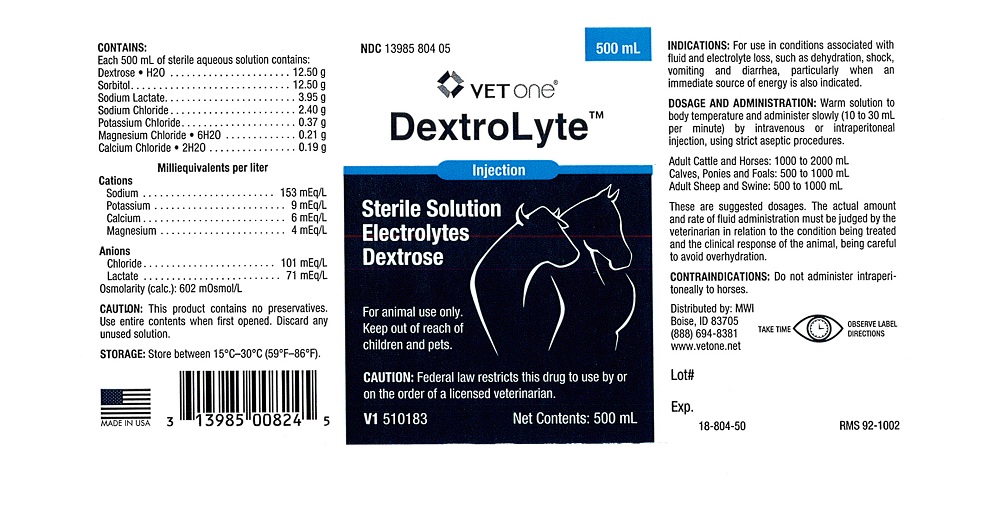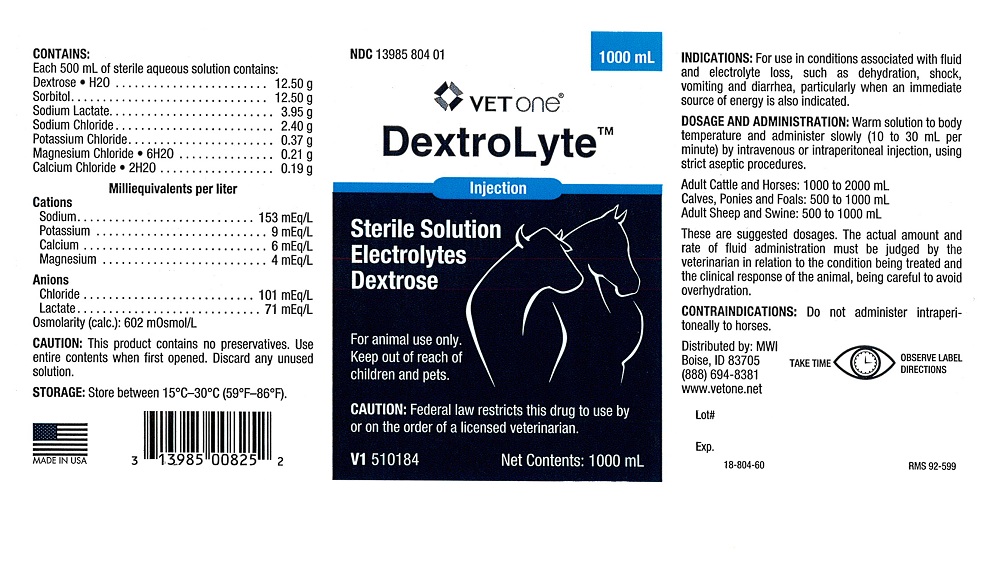 DRUG LABEL: DextroLyte
NDC: 13985-804 | Form: INJECTION, SOLUTION
Manufacturer: MWI (VetOne)
Category: animal | Type: PRESCRIPTION ANIMAL DRUG LABEL
Date: 20240813

ACTIVE INGREDIENTS: Dextrose Monohydrate 12.50 g/500 mL; Sorbitol 12.50 g/500 mL; Sodium Lactate 3.95 g/500 mL; Sodium Chloride 2.40 g/500 mL; Potassium Chloride 0.37 g/500 mL; Magnesium Chloride 0.21 g/500 mL; Calcium Chloride 0.19 g/500 mL

DextroLyte

VETERINARY INDICATIONS

For animal use only. Keep out of reach of children and pets.

CAUTION:

Federal law restricts this drug to use by or on the order of a licensed veterinarian.

INDICATIONS:

For use in conditions associated with fluid and electrolyte loss, such as dehydration, shock, vomiting and diarrhea, particularly when an immediate source of energy is also indicated.

DOSAGE AND ADMINISTRATION:

Warm solution to body temperature and administer slowly (10 to 30 mL per minute) by intravenous or intraperitoneal injection, using strict aseptic procedures.

Adult Cattle and Horses: 1000 to 2000 mL

Calves, Ponies and Foals: 500 to 1000 mL

Adult Sheep and Swine: 500 to 1000 mL

These are suggested dosages. The actual amount and rate of fluid administration must be judged by the veterinarian in relation to the condition being treated and the clinical response of the animal, being careful to avoid overhydration.

CONTRAINDICTIONS:

Do not administer intraperitoneally to horses.

CONTAINS:

Each 500 mL of sterile aqueous solution contains:

Dextrose.H2O...................................................12.50 g

Sorbitol.............................................................12.50 g

Sodium Lactate..................................................3.95 g

Sodium Chloride.................................................2.40 g

Potassium Chloride.............................................0.37 g

Magnesium Chloride.6H2O..................................0.21 g

Calcium Chloride.2H2O.......................................0.19 g

Milliequivalents per liter

Cations
Sodium ................................................. 153 mEq/L
Potassium................................................. 9 mEq/L
Calcium..................................................... 6 mEq/L
Magnesium................................................ 4 mEq/L
Anions
Chloride................................................. 101 mEq/L
Lactate................................................... 71 mEq/L
Osmolarity (calc.): 602 mOsmol/L

CAUTION:

This product contains no preservatives. Use entire contents when first opened. Discard any unused solution.

STORAGE:

Store between 15 degree C - 30 degree C (59 degree F - 86 degree F).